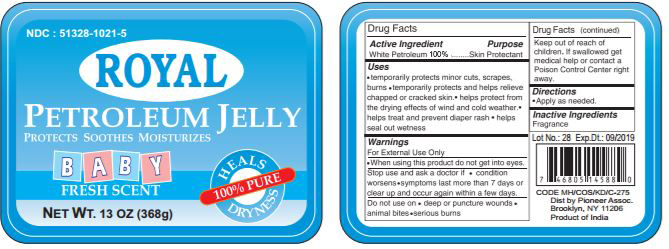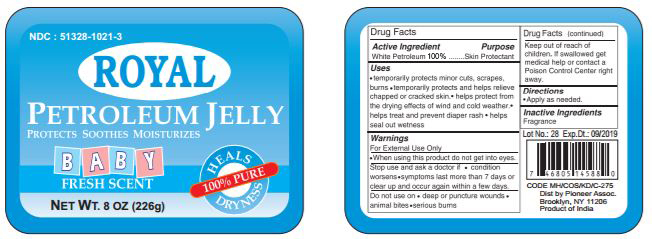 DRUG LABEL: Royal Petroleum Jelly Baby Fresh Scent Blue
NDC: 51328-1021 | Form: JELLY
Manufacturer: Royal Exports
Category: otc | Type: HUMAN OTC DRUG LABEL
Date: 20200129

ACTIVE INGREDIENTS: PETROLATUM 99.9 g/100 g
INACTIVE INGREDIENTS: WATER

Active Ingredient

White Petrolatum (99.9% w/w)

Purpose

Skin Protectant

Uses

- temporarily protects minor cuts, scrapes, burns
- temporarily protects and helps relieve chapped or cracked skin
- helps protect from effects of wind and cold weather
- helps treat and prevent diaper rash
- helps seal out wetness

Warnings

- FOR EXTERNAL USE ONLY

When using this product

- do not get into eyes

Stop use and ask a doctor if

- condition worsens
- symptoms last for more than 7 days or clear up and occur again within a few day

Do not use on

- deep or puncture wounds
- animal bites or serious burns

Keep out of reach of children

If swallowed, get medical help or contact a Poison Control Center right away

Directions

apply as needed

Inactive Ingredient

Fragrance